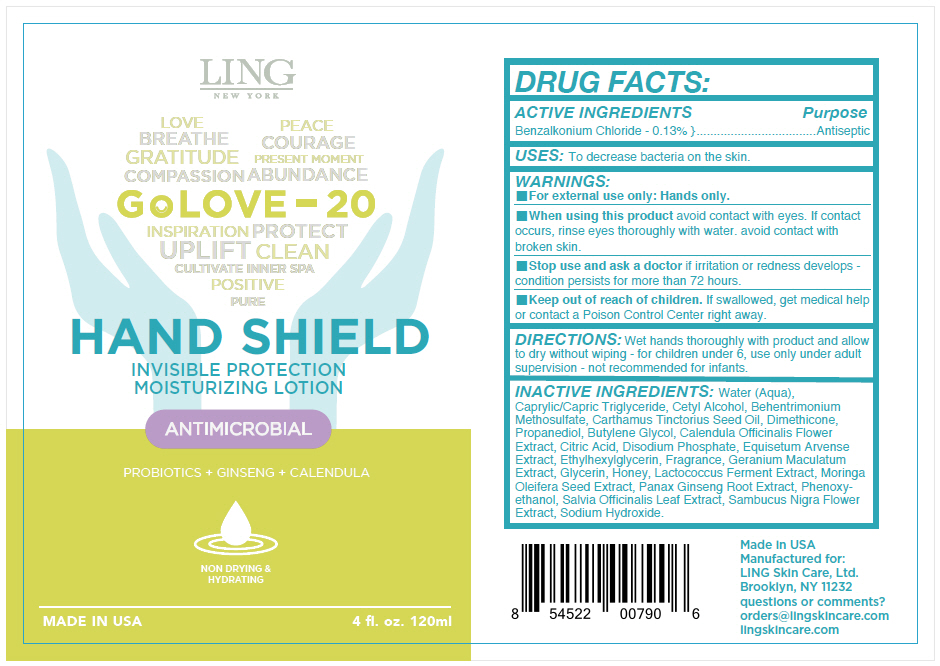 DRUG LABEL: LING New York - Hand Shield
NDC: 66163-2102 | Form: LOTION
Manufacturer: Cosmetic Solutions LLC
Category: otc | Type: HUMAN OTC DRUG LABEL
Date: 20210615

ACTIVE INGREDIENTS: BENZALKONIUM CHLORIDE 1.3 mg/10 mL
INACTIVE INGREDIENTS: Water; Medium-Chain Triglycerides; Cetyl Alcohol; Behentrimonium Methosulfate; Safflower Oil; Dimethicone; Propanediol; Butylene Glycol; Calendula Officinalis Flower; Citric Acid Monohydrate; Sodium Phosphate, Dibasic, Anhydrous; EQUISETUM ARVENSE BRANCH; Ethylhexylglycerin; GERANIUM MACULATUM ROOT; Glycerin; Honey; Asian Ginseng; Phenoxyethanol; Sambucus Nigra Flower; Sodium Hydroxide

LING New York - Hand Shield

DRUG FACTS:

ACTIVE INGREDIENTS

Benzalkonium Chloride - 0.13%

Purpose

Antiseptic

USES

To decrease bacteria on the skin.

WARNINGS

- For external use only: Hands only.

- When using this product avoid contact with eyes. If contact occurs, rinse eyes thoroughly with water. avoid contact with broken skin.

- Stop use and ask a doctor if irritation or redness develops - condition persists for more than 72 hours.

- Keep out of reach of children. If swallowed, get medical help or contact a Poison Control Center right away.

DIRECTIONS

Wet hands thoroughly with product and allow to dry without wiping - for children under 6, use only under adult supervision - not recommended for infants.

INACTIVE INGREDIENTS

Water (Aqua), Caprylic/Capric Triglyceride, Cetyl Alcohol, Behentrimonium Methosulfate, Carthamus Tinctorius Seed Oil, Dimethicone, Propanediol, Butylene Glycol, Calendula Officinalis Flower Extract, Citric Acid, Disodium Phosphate, Equisetum Arvense Extract, Ethylhexylglycerin, Fragrance, Geranium Maculatum Extract, Glycerin, Honey, Lactococcus Ferment Extract, Moringa Oleifera Seed Extract, Panax Ginseng Root Extract, Phenoxyethanol, Salvia Officinalis Leaf Extract, Sambucus Nigra Flower Extract, Sodium Hydroxide.

questions or comments?

orders@lingskincare.com
lingskincare.com

PRINCIPAL DISPLAY PANEL - 120 ml Bottle Label

LING
NEW YORK

LOVE
PEACE
BREATH
COURAGE
GRATITUDE
PRESENT MOMENT
COMPASSION
ABUNDANCE

Go LOVE – 20

INSPIRATION
PROTECT
UPLIFT
CLEAN
CULTIVATE INNER SPA
POSITIVE
PURE

HAND SHIELD

INVISIBLE PROTECTION
MOISTURIZING LOTION

ANTIMICROBIAL

PROBIOTICS + GINSENG + CALENDULA

NON DRYING &
HYDRATING

MADE IN USA

4 fl. oz. 120ml